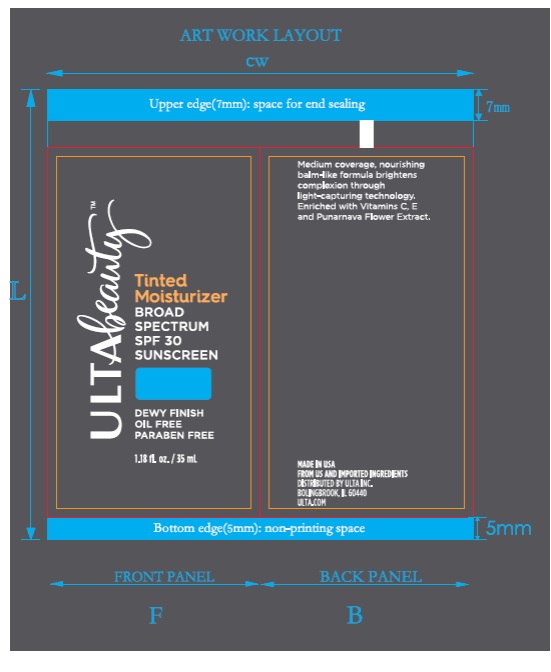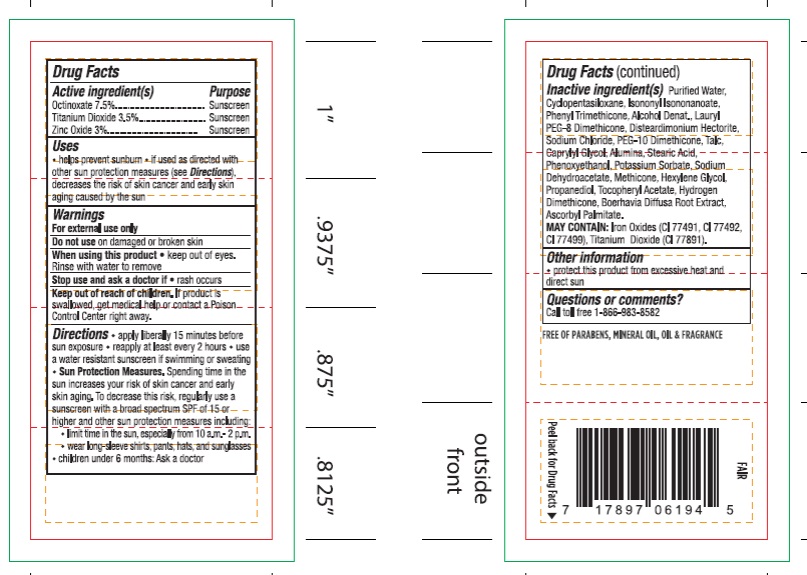 DRUG LABEL: ULTA BEAUTY TINTED MOISTURIZER
NDC: 62296-0118 | Form: LOTION
Manufacturer: Ulta
Category: otc | Type: HUMAN OTC DRUG LABEL
Date: 20170928

ACTIVE INGREDIENTS: OCTINOXATE 7.5 g/100 mL; TITANIUM DIOXIDE 3.5 g/100 mL; ZINC OXIDE 3 g/100 mL
INACTIVE INGREDIENTS: WATER; CYCLOMETHICONE 5; ISONONYL ISONONANOATE; PHENYL TRIMETHICONE; ALCOHOL; PEG-8 DIMETHICONE; DISTEARDIMONIUM HECTORITE; CAPRYLYL GLYCOL; ALUMINUM OXIDE; STEARIC ACID; PHENOXYETHANOL; POTASSIUM SORBATE; SODIUM DEHYDROACETATE; METHICONE (20 CST); HEXYLENE GLYCOL; PROPANEDIOL; .ALPHA.-TOCOPHEROL ACETATE; HYDROGEN DIMETHICONE (13 CST); BOERHAVIA DIFFUSA ROOT; ASCORBYL PALMITATE; FERRIC OXIDE RED; FERRIC OXIDE YELLOW; FERROSOFERRIC OXIDE

Active ingredient(s)

OCTINOXATE 7.5%

TITANIUM DIOXIDE 3.5%

ZINC OXIDE 3%

Purpose

Sunscreen

Uses

- helps prevent sunburn
- if used as directed with other sun protection measures (see Directions), decreases the risk of skin cancer and early skin aging caused by the sun

Warnings

For external use only

Do Not use

on damaged or broken skin

When using this product

- keep out of eyes. Rinse with water to remove.

stop use and ask a doctor

- if rash occurs.

keep out of reach of children

If product is swallowed, get medical help or contact a Poison Control Center right away.

- May stain some fabrics

Directions

- apply liberally 15 minutes before sun exposure
- reapply at least every 2 hours
- use a water resistant sunscreen if swimming or sweating.
- Sun Protection Measures. Spending time in the sun increases your risk of skin cancer and early skin aging. To decrease this risk, regularly use a sunscreen with a broad spectrum SPF of 15 or higher and other sun protection measures including:
- limit time in the sun, especially from 10 a.m. - 2 p.m.
- wear long-sleeve shirts, pants, hats, and sunglasses
- children under 6 months of age: Ask a doctor

Inactive Ingredients

Purified Water, Cyclopentasiloxane, Isononyl lsononanoate, Phenyl Trimethicone, Alcohol Denat., Lauryl PEG-8 Dimethieone, Disteardimonium Hectorite, Sodium Chloride, PEG-10 Dimethicone, Talc, Caprylyl Glycol, ALumina, Stearic Acid, Phenoxyethanol, Potassium Sorbate, Sodium Dehydroacetate, Methicone, Hexylene Glycol, Propanediol, Tocopheryl Acetate, Hydrogen Dimethicone, Boerhavia Diffusa Root Extract, Ascorbyl Palmitate.
MAY CONTAIN: Iron Oxides (CI 77491, CI 77492, CI77499), Titanium Dioxide (CI77891).

Other information

- protect this product from excessive heat and direct sun

QUESTIONS OR COMMENTS?

CALL TOLL FREE 1-866-983-8582